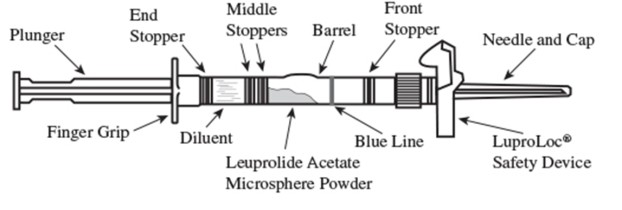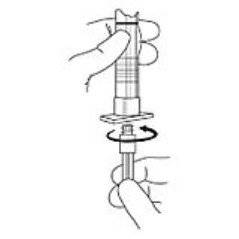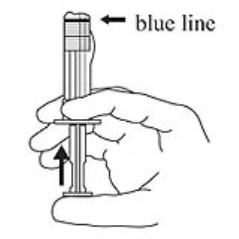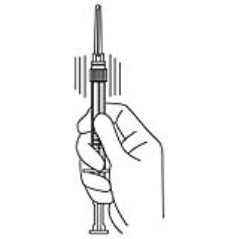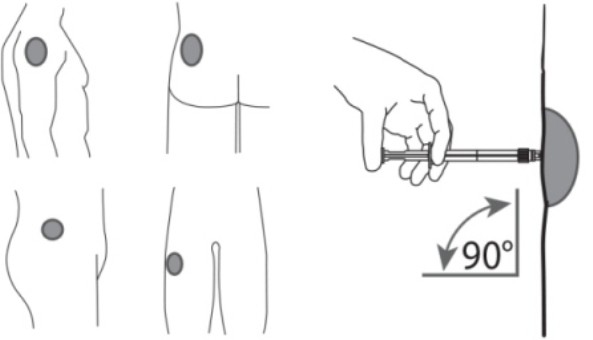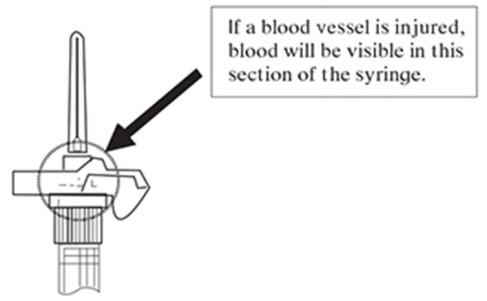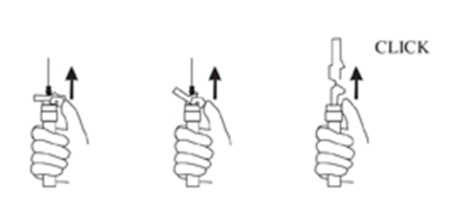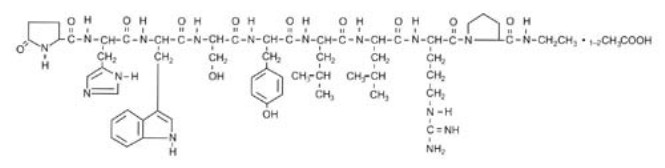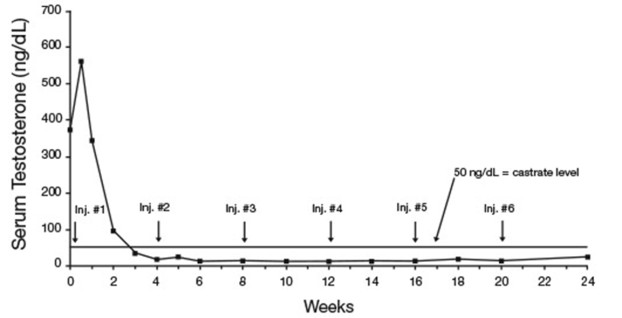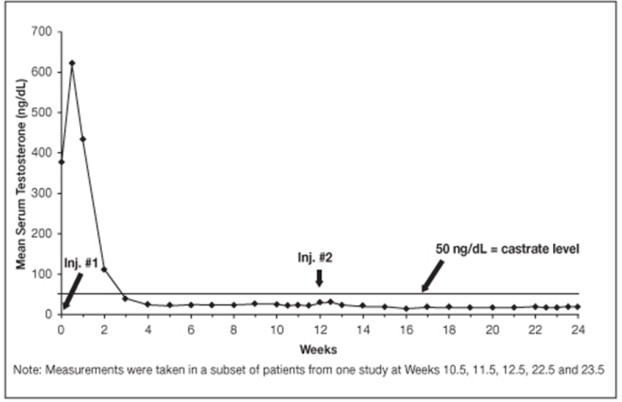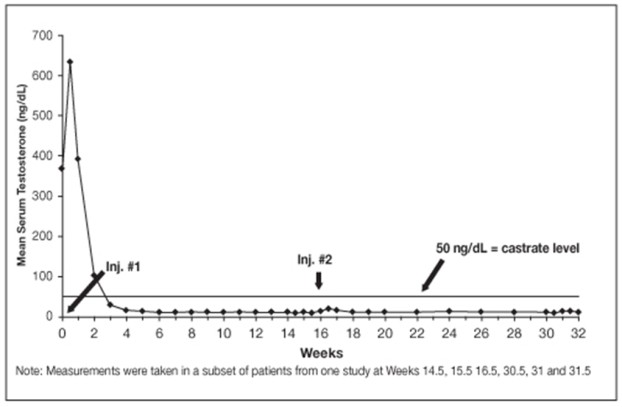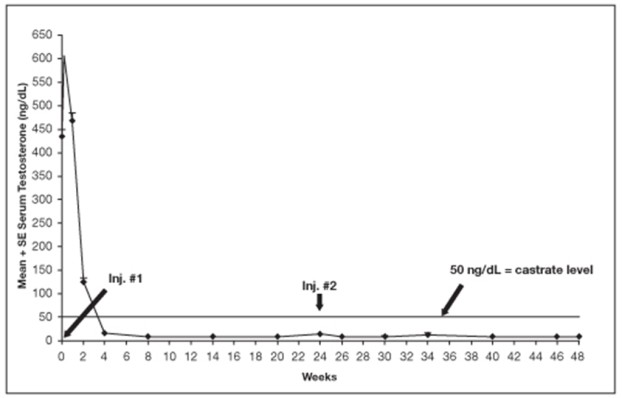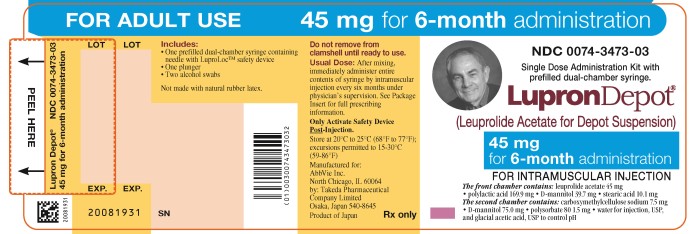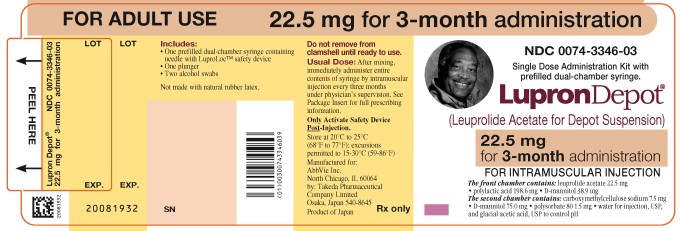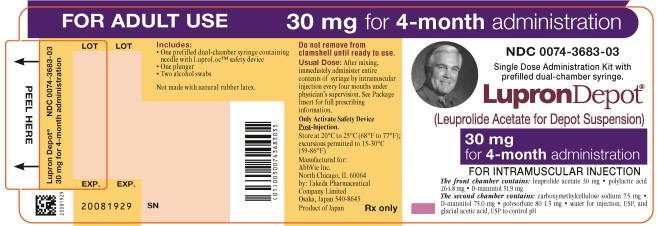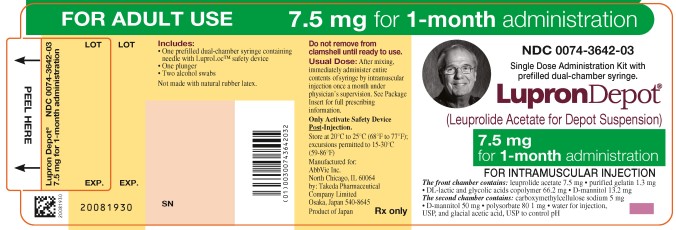 DRUG LABEL: Lupron Depot
NDC: 0074-3473 | Form: KIT | Route: INTRAMUSCULAR
Manufacturer: AbbVie Inc.
Category: prescription | Type: HUMAN PRESCRIPTION DRUG LABEL
Date: 20250818

ACTIVE INGREDIENTS: LEUPROLIDE ACETATE 45 mg/1.5 mL
INACTIVE INGREDIENTS: POLYLACTIDE 169.9 mg/1.5 mL; MANNITOL 114.7 mg/1.5 mL; STEARIC ACID 10.1 mg/1.5 mL; CARBOXYMETHYLCELLULOSE SODIUM, UNSPECIFIED FORM 7.5 mg/1.5 mL; POLYSORBATE 80 1.5 mg/1.5 mL; WATER; ACETIC ACID; ISOPROPYL ALCOHOL; WATER

HIGHLIGHTS OF PRESCRIBING INFORMATION

These highlights do not include all the information needed to use LUPRON DEPOT safely and effectively. See full prescribing information for LUPRON DEPOT.
LUPRON DEPOT (leuprolide acetate for depot suspension)
Initial U.S. Approval: 1989

RECENT MAJOR CHANGES

Dosage and Administration (2) | 8/2025
Dosage Forms and Strengths (3) | 8/2025

1 INDICATIONS AND USAGE

LUPRON DEPOT is a gonadotropin releasing hormone (GnRH) agonist indicated for:

- treatment of advanced prostate cancer. (1)

2 DOSAGE AND ADMINISTRATION

LUPRON DEPOT must be administered under the supervision of a physician. Due to different release characteristics, the dosage strengths are not additive and must be selected based upon the desired dosing schedule. (2)

- LUPRON DEPOT 7.5 mg for 1-month administration, given as a single intramuscular injection every 4 weeks. (2.1)
- LUPRON DEPOT 22.5 mg for 3-month administration, given as a single intramuscular injection every 12 weeks. (2.2)
- LUPRON DEPOT 30 mg for 4-month administration, given as a single intramuscular injection every 16 weeks. (2.3)
- LUPRON DEPOT 45 mg for 6-month administration, given as a single intramuscular injection every 24 weeks. (2.4)

3 DOSAGE FORMS AND STRENGTHS

7.5 mg, 22.5 mg, 30 mg, and 45 mg injections in a kit with prefilled dual chamber syringe. (3)

4 CONTRAINDICATIONS

- Hypersensitivity to GnRH, GnRH agonist or any of the excipients in LUPRON DEPOT. (4)

5 WARNINGS AND PRECAUTIONS

- Tumor Flare: Increased serum testosterone (~ 50% above baseline) may occur when initiating treatment with LUPRON DEPOT. Monitor for worsening of prostate cancer symptoms during the first few weeks of treatment. Monitor patients for increased bone pain, neuropathy, hematuria, ureteral obstruction, and spinal cord compression. Spinal cord compressions may contribute to paralysis with or without fatal complications. (5.1)
- Metabolic Syndrome: The use of GnRH agonists may lead to an increased risk of metabolic changes such as hyperglycemia, diabetes, hyperlipidemia, and non-alcoholic fatty liver disease. Monitor for signs and symptoms of metabolic syndrome including lipids, blood glucose level and/or HbA1c and manage according to current treatment guidelines. (5.2)
- Cardiovascular Diseases: Increased risk of myocardial infarction, sudden cardiac death and stroke has been reported in association with use of GnRH analogs in men. Monitor for cardiovascular disease and manage according to institutional guidelines. (5.3)
- Effect on QT/QTc Interval: Androgen deprivation therapy may prolong the QT interval. Consider risks and benefits. (5.4)
- Convulsions have been observed in patients with or without a history of predisposing factors. Manage convulsions according to institutional guidelines. (5.5)
- Severe Cutaneous Adverse Reactions (SCARs), including Stevens-Johnson syndrome/toxic epidermal necrolysis (SJS/TEN), occurred in patients treated with LUPRON DEPOT. Interrupt LUPRON DEPOT if signs or symptoms of SCARs develop. Permanently discontinue if SCARs are confirmed. (5.6)
- Embryo-Fetal Toxicity: LUPRON DEPOT may cause fetal harm. (5.8, 8.1)

6 ADVERSE REACTIONS

- LUPRON DEPOT 7.5 mg for 1-month administration: The most common adverse reactions (>10%) were general pain, hot flashes/sweats, GI disorders, edema, respiratory disorder, urinary disorder. (6.1)
- LUPRON DEPOT 22.5 mg for 3-month administration: The most common adverse reactions (>10%) were general pain, injection site reaction, hot flashes/sweats, GI disorders, joint disorders, testicular atrophy, urinary disorders. (6.2)
- LUPRON DEPOT 30 mg for 4-month administration: The most common adverse reactions (>10%) were asthenia, flu syndrome, general pain, headache, injection site reaction, hot flashes/sweats, GI disorders, edema, skin reaction, urinary disorders. (6.3)
- LUPRON DEPOT 45 mg for 6-month administration: The most common adverse reactions (>10%) were hot flush, injection site pain, upper respiratory infection, and fatigue. (6.4)

In postmarketing experience, mood swings, depression, rare reports of suicidal ideation and attempt, rare reports of pituitary apoplexy, and rare reports of serious drug-induced liver injury have been reported. (6.5)

To report SUSPECTED ADVERSE REACTIONS, contact AbbVie Inc.at 1-800-633-9110 or FDA at 1-800-FDA-1088 or www.fda.gov/medwatch

8 USE IN SPECIFIC POPULATIONS

- Females and males of reproductive potential: LUPRON DEPOT may impair fertility. Counsel patients on pregnancy planning and prevention. (8.3)
- Pediatric: These LUPRON DEPOT formulations are not indicated for use in children. See the LUPRON DEPOT PED® prescribing information for the use of leuprolide acetate in children with central precocious puberty.
- Geriatric: This label reflects clinical trials for LUPRON DEPOT in prostate cancer in which the majority of the subjects studied were at least 65 years of age.

FULL PRESCRIBING INFORMATION

1 INDICATIONS AND USAGE

LUPRON DEPOT 7.5 mg for 1-month administration, 22.5 mg for 3-month administration, 30 mg for 4-month administration, and 45 mg for 6-month administration (leuprolide acetate) are indicated for the treatment of advanced prostate cancer.

2 DOSAGE AND ADMINISTRATION

LUPRON DEPOT must be administered by a healthcare provider.

In patients treated with GnRH analogues for prostate cancer, treatment is usually continued upon development of non-metastatic and metastatic castration-resistant prostate cancer.

Table 1. LUPRON DEPOT Recommended Dosing
Dosage | 7.5 mg for 1-Month Administration | 22.5 mg for 3-Month Administration | 30 mg for 4-Month Administration | 45 mg for 6-Month Administration
Recommended dose | 1 injection every 4 weeks | 1 injection every 12 weeks | 1 injection every 16 weeks | 1 injection every 24 weeks

2.1 LUPRON DEPOT 7.5 mg for 1-Month Administration

The recommended dose of LUPRON DEPOT 7.5 mg for 1-month administration is one injection every 4 weeks. Do not use concurrently a fractional dose, or a combination of doses of this or any depot formulation due to different release characteristics.

Incorporated in a depot formulation, the lyophilized microspheres must be reconstituted and should be administered every 4 weeks as a single intramuscular injection.

For optimal performance of the prefilled dual chamber syringe (PDS), read and follow the instructions in Section 2.5.

2.2 LUPRON DEPOT 22.5 mg for 3-Month Administration

The recommended dose of LUPRON DEPOT 22.5 mg for 3-month administration is one injection every 12 weeks. Do not use concurrently a fractional dose, or a combination of doses of this or any depot formulation due to different release characteristics.

Incorporated in a depot formulation, the lyophilized microspheres must be reconstituted and should be administered every 12 weeks as a single intramuscular injection.

For optimal performance of the prefilled dual chamber syringe (PDS), read and follow the instructions in Section 2.5.

2.3 LUPRON DEPOT 30 mg for 4-Month Administration

The recommended dose of LUPRON DEPOT 30 mg for 4-month administration is one injection every 16 weeks. Do not use concurrently a fractional dose, or a combination of doses of this or any depot formulation due to different release characteristics.

Incorporated in a depot formulation, the lyophilized microspheres must be reconstituted and should be administered every 16 weeks as a single intramuscular injection.

For optimal performance of the prefilled dual chamber syringe (PDS), read and follow the instructions in Section 2.5.

2.4 LUPRON DEPOT 45 mg for 6-Month Administration

The recommended dose of LUPRON DEPOT 45 mg for 6-month administration is one injection every 24 weeks. Do not use concurrently a fractional dose, or a combination of doses of this or any depot formulation due to different release characteristics.

Incorporated in a depot formulation, the lyophilized microspheres must be reconstituted and should be administered every 24 weeks as a single intramuscular injection.

For optimal performance of the prefilled dual chamber syringe (PDS), read and follow the instructions in Section 2.5.

2.5 Reconstitution and Administration for Injection of LUPRON DEPOT

- Reconstitute and administer the lyophilized microspheres as a single intramuscular injection.
- Inject the suspension immediately or discard if not used within two hours, because LUPRON DEPOT does not contain a preservative.

1. Visually inspect the LUPRON DEPOT powder. DO NOT USE the syringe if clumping or caking is evident. A thin layer of powder on the wall of the syringe is considered normal prior to mixing with the diluent. The diluent should appear clear and colorless.

2. To prepare for injection, screw the white plunger into the end stopper until the stopper begins to turn (see Figure 1 and Figure 2).

Figure 1

Figure 2

3. Hold the syringe UPRIGHT. Release the diluent by SLOWLY PUSHING (6 to 8 seconds) the plunger until the first middle stopper is at the blue line in the middle of the barrel (see Figure 3).

Figure 3

4. Keep the syringe UPRIGHT. Mix the microspheres (powder) thoroughly by gently shaking the syringe until the powder forms a uniform suspension. The suspension will appear milky. If the powder adheres to the stopper or caking/clumping is present, tap the syringe with your finger to disperse. DO NOT USE if any of the powder has not gone into suspension (see Figure 4).

Figure 4

5. Keep the syringe UPRIGHT. With the opposite hand pull the needle cap upward without twisting.

6. Keep the syringe UPRIGHT. Advance the plunger to expel the air from the syringe. Now the syringe is ready for injection.

7. After cleaning the injection site with an alcohol swab, administer the intramuscular injection by inserting the needle at a 90 degree angle into the gluteal area, anterior thigh, or deltoid; injection sites should be alternated (see Figure 5).

Figure 5

NOTE: If a blood vessel is accidentally penetrated, aspirated blood will be visible just below the luer lock (see Figure 6) and can be seen through the transparent LuproLoc® safety device. If blood is present, remove the needle immediately. Do not inject the medication.

Figure 6

8. Inject the entire contents of the syringe intramuscularly.

9. Withdraw the needle. Once the syringe has been withdrawn, immediately activate the LuproLoc® safety device by pushing the arrow on the lock upward towards the needle tip with the thumb or finger, as illustrated, until the needle cover of the safety device over the needle is fully extended and a CLICK is heard or felt (see Figure 7).

Figure 7

10. Dispose of the syringe according to local regulations/procedures.

3 DOSAGE FORMS AND STRENGTHS

LUPRON DEPOT 7.5 mg for 1-month administration, 22.5 mg for 3-month administration, 30 mg for 4-month administration, and 45 mg for 6-month administration are each supplied as a kit with a prefilled single-dose dual chamber syringe containing white lyophilized microsphere powder in one chamber and a clear, colorless diluent for reconstitution in the other chamber.

4 CONTRAINDICATIONS

LUPRON DEPOT is contraindicated in:

- Hypersensitivity

LUPRON DEPOT is contraindicated in individuals with known hypersensitivity to GnRH agonists or any of the excipients in LUPRON DEPOT. Reports of anaphylactic reactions to GnRH agonists have been reported in the medical literature.

5 WARNINGS AND PRECAUTIONS

5.1 Tumor Flare

Initially, LUPRON DEPOT, like other GnRH agonists, causes increases in serum levels of testosterone to approximately 50% above baseline during the first weeks of treatment. Patients may experience worsening of symptoms or onset of new signs and symptoms during the first few weeks of treatment, including bone pain, neuropathy, hematuria, or bladder outlet obstruction. Spinal cord compression may contribute to paralysis with or without fatal complications.

Monitor patients for tumor flare symptoms during the first few weeks of treatment with LUPRON DEPOT. Closely monitor patients with metastatic vertebral lesions and/or with urinary tract obstruction for new or worsening symptoms.

5.2 Metabolic Syndrome

The use of GnRH agonists may lead to metabolic changes such as hyperglycemia, diabetes mellitus, and hyperlipidemia. Non-alcoholic fatty liver disease, including cirrhosis, occurred in the post-marketing setting. Hyperglycemia may represent new-onset diabetes mellitus or worsening of glycemic control in patients with pre-existing diabetes. Monitor for changes in serum lipids, blood glucose and/or glycosylated hemoglobin (HbA1c) in patients receiving a GnRH agonist, and manage according to current treatment guidelines.

5.3 Cardiovascular Diseases

Increased risk of developing myocardial infarction, sudden cardiac death and stroke has been reported in association with use of GnRH agonists in men. The risk appears low based on the reported odds ratios, and should be evaluated carefully along with cardiovascular risk factors when determining a treatment for patients with prostate cancer. Patients receiving a GnRH agonist should be monitored for symptoms and signs suggestive of development of cardiovascular disease and be managed according to institutional guidelines.

5.4 Effect on QT/QTc Interval

Androgen deprivation therapy may prolong the QT/QTc interval. Providers should consider whether the benefits of androgen deprivation therapy outweigh the potential risks in patients with congenital long QT syndrome, congestive heart failure, frequent electrolyte abnormalities, and in patients taking drugs known to prolong the QT interval. Electrolyte abnormalities should be corrected. Consider periodic monitoring of electrocardiograms and electrolytes.

5.5 Convulsions

Postmarketing reports of convulsions have been observed in patients on leuprolide acetate therapy. These included patients with a history of seizures, epilepsy, cerebrovascular disorders, central nervous system anomalies or tumors, and in patients on concomitant medications that have been associated with convulsions such as bupropion and SSRIs. Convulsions have also been reported in patients in the absence of any of the conditions mentioned above. Patients receiving a GnRH agonist who experience convulsion should be managed according to institutional guidelines.

5.6 Severe Cutaneous Adverse Reactions

Severe cutaneous adverse reactions (SCARs), including Stevens-Johnson syndrome/toxic epidermal necrolysis (SJS/TEN), drug reaction with eosinophilia and systemic symptoms (DRESS), and acute generalized exanthematous pustulosis (AGEP), occurred in patients receiving LUPRON DEPOT; including cases with visceral involvement and/or requiring skin grafts [see Adverse Reactions (6.5)].

Monitor patients for the development of SCARs. Advise patients of the signs and symptoms of SCARs (e.g., a prodrome of fever, flu-like symptoms, mucosal lesions, progressive skin rash, or lymphadenopathy).

If a SCAR is suspected, interrupt LUPRON DEPOT until the etiology of the reaction has been determined. Consultation with a dermatologist is recommended. If a SCAR is confirmed, or for other grade 4 skin reactions, permanently discontinue LUPRON DEPOT.

5.7 Laboratory Tests

Monitor serum levels of testosterone following injection of LUPRON DEPOT 7.5 mg for 1-month administration, 22.5 mg for 3-month administration, 30 mg for 4-month administration, or 45 mg for 6-month administration. In the majority of patients, testosterone levels increased above baseline, and then declined thereafter to castrate levels (< 50 ng/dL) within four weeks. [see Clinical Studies (14) and Adverse Reactions (6)].

5.8 Embryo-Fetal Toxicity

Based on findings in animal studies, LUPRON DEPOT may cause fetal harm when administered to a pregnant woman. In animal developmental and reproductive toxicology studies, administration of the monthly formulation of leuprolide acetate on day 6 of pregnancy (sustained exposure was expected throughout the period of organogenesis) caused adverse embryo-fetal toxicity in animals at doses less than the human dose, based on body surface area, using an estimated daily dose. Advise pregnant patients and females of reproductive potential of the potential risk to the fetus [see Use in Specific Populations (8.1)].

6 ADVERSE REACTIONS

The following is discussed in more detail in other sections of the labeling:

- Tumor Flare [see Warnings and Precautions (5.1)]
- Metabolic Syndrome [see Warnings and Precautions (5.2)]
- Cardiovascular Disease [see Warnings and Precautions (5.3)]
- Effect on QT/QTc Interval [see Warnings and Precautions (5.4)]
- Convulsions [see Warnings and Precautions (5.5)]
- Severe Cutaneous Adverse Reactions [see Warnings and Precautions (5.6)]

Because clinical trials are conducted under widely varying conditions, adverse reaction rates observed in the clinical trials of a drug cannot be directly compared to rates in the clinical trials of another drug and may not reflect the rates observed in practice.

6.1 LUPRON DEPOT 7.5 mg for 1-Month Administration

In the majority of patients testosterone levels increased above baseline during the first week, declining thereafter to baseline levels or below by the end of the second week of treatment.

Potential exacerbations of signs and symptoms during the first few weeks of treatment is a concern in patients with vertebral metastases and/or urinary obstruction or hematuria which, if aggravated, may lead to neurological problems such as temporary weakness and/or paresthesia of the lower limbs or worsening of urinary symptoms [see Warnings and Precautions (5.1)].

In a clinical trial of LUPRON DEPOT 7.5 mg for 1-month administration, the following adverse reactions were reported in 5% or more of the patients during the initial 24-week treatment period.

Table 2. Adverse Reactions Reported in ≥ 5% of Patients
LUPRON DEPOT 7.5 mg for 1-Month Administration (N=56)
 | N | (%)
Body As A Whole
General pain | 13 | (23.2)
Infection | 3 | (5.4)
Cardiovascular System
Hot flashes/sweats* | 32 | (57.1)
Digestive System
GI disorders | 8 | (14.3)
Metabolic and Nutritional Disorders
Edema | 8 | (14.3)
Nervous System
Libido decreased* | 3 | (5.4)
Respiratory System
Respiratory disorder | 6 | (10.7)
Urogenital System
Urinary disorder | 7 | (12.5)
Impotence* | 3 | (5.4)
Testicular atrophy* | 3 | (5.4)
* Due to the expected physiologic effect of decreased testosterone levels.

In this same study, the following adverse reactions were reported in less than 5% of the patients on LUPRON DEPOT 7.5 mg for 1-month administration.

Body As A Whole - asthenia, cellulitis, fever, headache, injection site reaction, neoplasm

Cardiovascular System - angina, congestive heart failure

Digestive System - anorexia, dysphagia, eructation, peptic ulcer

Blood and Lymphatic System - ecchymosis

Musculoskeletal System - myalgia

Nervous System - agitation, insomnia/sleep disorders, neuromuscular disorders

Respiratory System - emphysema, hemoptysis, lung edema, sputum increased

Skin and Appendages - hair disorder, skin reaction

Urogenital System - balanitis, breast enlargement, urinary tract infection

Laboratory Abnormalities

Abnormalities of certain parameters were observed, but their relationship to drug treatment are difficult to assess in this population. The following were recorded in ≥5% of patients at final visit: Decreased albumin, decreased hemoglobin/hematocrit, decreased prostatic acid phosphatase, decreased total protein, decreased urine specific gravity, hyperglycemia, hyperuricemia, increased BUN, increased creatinine, increased liver function tests (AST, LDH), increased phosphorus, increased platelets, increased prostatic acid phosphatase, increased total cholesterol, increased urine specific gravity, leukopenia.

6.2 LUPRON DEPOT 22.5 mg for 3-Month Administration

In two clinical trials of LUPRON DEPOT 22.5 mg for 3-month administration, the following adverse reactions were reported to have a possible or probable relationship to drug as ascribed by the treating physician in 5% or more of the patients receiving the drug.

Table 3. Adverse Reactions Reported in ≥ 5% of Patients
LUPRON DEPOT 22.5 mg for 3-Month Administration
Body System/Reaction | N=94 | (%)
Body As A Whole
Asthenia | 7 | (7.4)
General pain | 25 | (26.6)
Headache | 6 | (6.4)
Injection site reaction | 13 | (13.8)
Cardiovascular System
Hot flashes/sweats | 55 | (58.5)
Digestive System
GI disorders | 15 | (16.0)
Musculoskeletal System
Joint disorders | 11 | (11.7)
Central/Peripheral Nervous System
Dizziness/vertigo | 6 | (6.4)
Insomnia/sleep disorders | 8 | (8.5)
Neuromuscular disorders | 9 | (9.6)
Respiratory System
Respiratory disorders | 6 | (6.4)
Skin and Appendages
Skin reaction | 8 | (8.5)
Urogenital System
Testicular atrophy | 19 | (20.2)
Urinary disorders | 14 | (14.9)

In these same studies, the following adverse reactions were reported in less than 5% of the patients on LUPRON DEPOT 22.5 mg for 3-month administration.

Body As A Whole - enlarged abdomen, fever

Cardiovascular System - arrhythmia, bradycardia, heart failure, hypertension, hypotension, varicose vein

Digestive System - anorexia, duodenal ulcer, increased appetite, thirst/dry mouth

Blood and Lymphatic System - anemia, lymphedema

Metabolic and Nutritional Disorders - dehydration, edema

Central/Peripheral Nervous System - anxiety, delusions, depression, hypesthesia, libido decreased*, nervousness, paresthesia

Respiratory System - epistaxis, pharyngitis, pleural effusion, pneumonia

Special Senses - abnormal vision, amblyopia, dry eyes, tinnitus

Urogenital System - gynecomastia, impotence*, penis disorders, testis disorders.

* Physiologic effect of decreased testosterone.

Laboratory Abnormalities

Abnormalities of certain parameters were observed, but are difficult to assess in this population. The following were recorded in ≥5% of patients: increased BUN, hyperglycemia, hyperlipidemia (total cholesterol, LDL-cholesterol, triglycerides), hyperphosphatemia, abnormal liver function tests, increased PT, increased PTT. Additional laboratory abnormalities reported were: decreased platelets, decreased potassium and increased WBC.

6.3 LUPRON DEPOT 30 mg for 4-Month Administration

The 4-month formulation of LUPRON DEPOT 30 mg was utilized in clinical trials that studied the drug in 49 nonorchiectomized prostate cancer patients for 32 weeks or longer and in 24 orchiectomized prostate cancer patients for 20 weeks.

In the above described clinical trials, the following adverse reactions were reported in ≥ 5% of the patients during the treatment period.

Table 4. Adverse Reactions Reported in ≥ 5% of Patients
LUPRON DEPOT 30 mg for 4-Month Administration
Body System/Events | Nonorchiectomized |  | Orchiectomized
 | Study 013 |  | Study 012
 | N=49 | (%) | N=24 | (%)
Body As A Whole
Asthenia | 6 | (12.2) | 1 | (4.2)
Flu syndrome | 6 | (12.2) | 0 | (0.0)
General pain | 16 | (32.7) | 1 | (4.2)
Headache | 5 | (10.2) | 1 | (4.2)
Injection site reaction | 4 | (8.2) | 9 | (37.5)
Cardiovascular System
Hot flashes/sweats | 23 | (46.9) | 2 | (8.3)
Digestive System
GI disorders | 5 | (10.2) | 3 | (12.5)
Metabolic and Nutritional Disorders
Dehydration | 4 | (8.2) | 0 | (0.0)
Edema | 4 | (8.2) | 5 | (20.8)
Musculoskeletal System
Joint disorder | 8 | (16.3) | 1 | (4.2)
Myalgia | 4 | (8.2) | 0 | (0.0)
Nervous System
Dizziness/vertigo | 3 | (6.1) | 2 | (8.3)
Neuromuscular disorders | 3 | (6.1) | 1 | (4.2)
Paresthesia | 4 | (8.2) | 1 | (4.2)
Respiratory System
Respiratory disorder | 4 | (8.2) | 1 | (4.2)
Skin and Appendages
Skin reaction | 6 | (12.2) | 0 | (0.0)
Urogenital System
Urinary disorders | 5 | (10.2) | 4 | (16.7)

In these same studies, the following adverse reactions were reported in less than 5% of the patients on LUPRON DEPOT 30 mg for 4-month administration.

Body As A Whole - abscess, accidental injury, allergic reaction, cyst, fever, generalized edema, hernia, neck pain, neoplasm

Cardiovascular System - atrial fibrillation, deep thrombophlebitis, hypertension

Digestive System - anorexia, eructation, gastrointestinal hemorrhage, gingivitis, gum hemorrhage, hepatomegaly, increased appetite, intestinal obstruction, periodontal abscess

Blood and Lymphatic System - lymphadenopathy

Metabolic and Nutritional Disorders - healing abnormal, hypoxia, weight loss

Musculoskeletal System - leg cramps, pathological fracture, ptosis

Nervous System - abnormal thinking, amnesia, confusion, convulsion, dementia, depression, insomnia/sleep disorders, libido decreased*, neuropathy, paralysis

Respiratory System - asthma, bronchitis, hiccup, lung disorder, sinusitis, voice alteration

Skin and Appendages - herpes zoster, melanosis

Urogenital System - bladder carcinoma, epididymitis, impotence*, prostate disorder, testicular atrophy*, urinary incontinence, urinary tract infection.

* Physiologic effect of decreased testosterone.

Laboratory Abnormalities

Abnormalities of certain parameters were observed, but their relationship to drug treatment is difficult to assess in this population. The following were recorded in ≥ 5% of patients: decreased bicarbonate, decreased hemoglobin/hematocrit/RBC, hyperlipidemia (total cholesterol, LDL-cholesterol, triglycerides), decreased HDL-cholesterol, eosinophilia, increased glucose, increased liver function tests (ALT, AST, GGTP, LDH), increased phosphorus. Additional laboratory abnormalities were reported: increased BUN and PT, leukopenia, thrombocytopenia, uricaciduria.

6.4 LUPRON DEPOT 45 mg for 6-Month Administration

One open label, multicenter study was conducted with LUPRON DEPOT 45 mg for 6-month administration in 151 prostate cancer patients. Patients were treated for 48 weeks, with 139/151 receiving two injections 24 weeks apart.

In the above described clinical trial, the following adverse reactions were reported in ≥ 5% of the patients during the treatment period. The Table 5 includes all adverse reactions reported in ≥ 5% of patients as well as the incidences of these adverse reactions that were considered, by the treating physician, to have a definite or possible relationship to LUPRON DEPOT.

Table 5. Adverse Reactions in ≥ 5% of Patients
LUPRON DEPOT 45 mg for 6-Month Administration
 | Treatment Emergent |  | Treatment Related
Adverse Event | N = 151 | (%) | N = 151 | (%)
Hot flush/flushing | 89 | 58.9 | 88 | 58.3
Injection site pain/discomfort | 29 | 19.2 | 16 | 10.6
Upper respiratory tract infection/influenza-like illness^1 | 32 | 21.2 | 0 | 0
Fatigue/lethargy | 20 | 13.2 | 18 | 11.9
Constipation | 15 | 9.9 | 5 | 3.3
Arthralgia | 14 | 9.3 | 2 | 1.3
Insomnia/sleep disorder | 13 | 8.6 | 5 | 3.3
Headache/sinus headache | 12 | 7.9 | 3 | 2.0
Musculoskeletal pain/ myalgia | 12 | 7.9 | 3 | 2.0
Second primary neoplasm^2 | 11 | 7.3 | 0 | 0
Cough | 10 | 6.6 | 2 | 1.3
Hematuria/hemorrhagic cystitis | 10 | 6.6 | 0 | 0
Hypertension/BP increased | 10 | 6.6 | 3 | 2.0
Rash | 9 | 6.0 | 3 | 2.0
Dysuria | 9 | 6.0 | 1 | 0.7
Urinary tract infection/cystitis | 9 | 6.0 | 0 | 0
Anemia/hemoglobin decreased | 10 | 6.6 | 2 | 1.3
Back pain | 8 | 5.3 | 0 | 0
COPD | 8 | 5.3 | 0 | 0
Dizziness | 8 | 5.3 | 3 | 2.0
Dyspnea/dyspnea on exertion | 8 | 5.3 | 2 | 1.3
Nocturia | 8 | 5.3 | 2 | 1.3
Peripheral/pitting edema | 8 | 5.3 | 2 | 1.3
Coronary artery disease/angina | 8 | 5.3 | 1 | 0.7

^1Includes influenza, nasal congestion, nasopharyngitis, rhinorrhea, upper respiratory tract infection, and viral upper respiratory tract infection

^2Includes basal cell carcinoma, bladder transitional cell carcinoma, lung neoplasm, malignant melanoma, non-Hodgkin’s lymphoma, and squamous cell carcinoma

The following adverse reactions led to discontinuation; fatigue, hot flush, second primary neoplasm, asthenia, coronary artery disease, constipation, hyperkalemia, and sleep disorder. Serious adverse reactions in ≥ 2% of patients, regardless of causality, included chronic obstructive pulmonary disease, coronary artery disease/angina, cerebrovascular accident/transient ischemic attack, pneumonia, and second primary neoplasms.

Laboratory Abnormalities

At baseline, 13.9% of patients had a CTCAE v4.0 grade 1 or 2 decreased hemoglobin. During the study, 42.4% of subjects had grade 1 decreased hemoglobin (10 - <12-5 g/dL), 2.0% had grade 2 (8 - <10 g/dL) and 1.3% of subjects had grade 3 or 4 (<8 g/dL). Likewise, 28.5% of patients had a grade 1 or 2 increased cholesterol at baseline while 55.0% had grade 1 increased cholesterol (>199- 300 mg/dL), 3.3% had a grade 2 increase (>300-400 mg/dL), and 0.7% of subjects had grade 3 (>400 mg/dL) during the study.

6.5 Postmarketing

The following adverse reactions have been identified during post-approval use of LUPRON DEPOT. Because these reactions are reported voluntarily from a population of uncertain size, it is not always possible to reliably estimate their frequency or establish a causal relationship to drug exposure.

During postmarketing surveillance, which includes other dosage forms and other patient populations, the following adverse reactions were reported.

Mood swings, including depression, have been reported. There have been very rare reports of suicidal ideation and attempt. Many, but not all, of these patients had a history of depression or other psychiatric illness. Patients should be counseled on the possibility of development or worsening of depression during treatment with LUPRON DEPOT.

Symptoms consistent with an anaphylactoid or asthmatic process have occurred (incidence rate of about 0.002%).

Changes in Bone Density - Decreased bone density has been reported in the medical literature in men who have had orchiectomy or who have been treated with a GnRH agonist analog. In a clinical trial, 25 men with prostate cancer, 12 of whom had been treated previously with leuprolide acetate for at least six months, underwent bone density studies as a result of pain. The leuprolide-treated group had lower bone density scores than the nontreated control group. It can be anticipated that long periods of medical castration in men will have effects on bone density.

Pituitary Apoplexy - During post-marketing surveillance, rare cases of pituitary apoplexy (a clinical syndrome secondary to infarction of the pituitary gland) have been reported after the administration of gonadotropin-releasing hormone agonists. In a majority of these cases, a pituitary adenoma was diagnosed, with a majority of pituitary apoplexy cases occurring within 2 weeks of the first dose, and some within the first hour. In these cases, pituitary apoplexy has presented as sudden headache, vomiting, visual changes, ophthalmoplegia, altered mental status, and sometimes cardiovascular collapse. Immediate medical attention has been required.

Symptoms consistent with fibromyalgia (e.g., joint and muscle pain, headaches, sleep disorders, gastrointestinal distress, and shortness of breath) have been reported individually and collectively.

Cardiovascular System - hypotension, myocardial infarction, pulmonary embolism

Respiratory, Thoracic and Mediastinal disorder - interstitial lung disease

Hepato-biliary disorder - serious drug-induced liver injury, non-alcoholic fatty liver disease

Skin reactions - rash, urticaria, photosensitivity, erythema multiforme, bullous dermatitis, dermatitis exfoliative, DRESS, SJS/ TEN, and AGEP

Blood and Lymphatic System - decreased WBC

Central/Peripheral Nervous System - convulsion, peripheral neuropathy, spinal fracture/paralysis

Endocrine System - diabetes mellitus

Musculoskeletal System - tenosynovitis-like symptoms

Urogenital System - prostate pain

General disorders and administration site conditions – injection site reactions including induration, abscess, and necrosis

See other LUPRON DEPOT and LUPRON Injection prescribing information for other reactions reported in women and pediatric populations.

7 DRUG INTERACTIONS

7.1 Drug/Laboratory Test Interactions

Administration of LUPRON DEPOT in therapeutic doses results in suppression of the pituitary-gonadal system. Normal function is usually restored within three months after treatment is discontinued. Due to the suppression of the pituitary-gonadal system by LUPRON DEPOT, diagnostic tests of pituitary gonadotropic and gonadal functions conducted during treatment and up to three months after discontinuation of LUPRON DEPOT may be affected.

8 USE IN SPECIFIC POPULATIONS

8.1 Pregnancy

Risk Summary

Based on findings in animal studies and mechanism of action, LUPRON DEPOT may cause fetal harm when administered to a pregnant woman [see Clinical Pharmacology (12.1)]. There are no available data in pregnant women to inform the drug-associated risk. In animal developmental and reproductive toxicology studies, administration of a monthly formulation of leuprolide acetate on day 6 of pregnancy (sustained exposure was expected throughout the period of organogenesis) caused adverse embryo-fetal toxicity in animals at doses less than the human dose based on body surface area using an estimated daily dose (see data). Advise pregnant patients and females of reproductive potential of the potential risk to the fetus.

Data

Animal Data

Major fetal malformations were observed in developmental and reproductive toxicology studies in rabbits after a single administration of the monthly formulation of leuprolide acetate on day 6 of pregnancy at doses of 0.00024, 0.0024, and 0.024 mg/kg (approximately 1/1600 to 1/16 the human dose based on body surface area using an estimated daily dose in animals and humans). Since a depot formulation was utilized in the study, a sustained exposure to leuprolide was expected throughout the period of organogenesis and to the end of gestation. Similar studies in rats did not demonstrate an increase in fetal malformations, however, there was increased fetal mortality and decreased fetal weights with the two higher doses of the monthly formulation of leuprolide acetate in rabbits and with the highest dose (0.024 mg/kg) in rats.

8.2 Lactation

The safety and efficacy of LUPRON DEPOT have not been established in females. There is no information regarding the presence of LUPRON DEPOT in human milk, the effects on the breastfed child, or the effects on milk production. Because many drugs are excreted in human milk and because of the potential for serious adverse reactions in a breastfed child from LUPRON DEPOT, a decision should be made to discontinue breastfeeding or discontinue the drug, taking into account the importance of the drug to the mother.

8.3 Females and Males of Reproductive Potential

Infertility

Males

Based on findings in animals and mechanism of action, LUPRON DEPOT may impair fertility in males of reproductive potential [see Nonclinical Toxicology (13.1)].

8.4 Pediatric Use

See LUPRON DEPOT-PED® (leuprolide acetate for depot suspension) labeling for the safety and effectiveness in children with central precocious puberty.

8.5 Geriatric Use

In the clinical trials for LUPRON DEPOT in prostate cancer 80% of the subjects studied were at least 65 years of age. Therefore, the labeling reflects the efficacy and safety of LUPRON DEPOT in this population.

10 OVERDOSAGE

There is no experience of overdosage in clinical trials. In rats, a single subcutaneous dose of 100 mg/kg (approximately 4,000 times the estimated daily human dose based on body surface area), resulted in dyspnea, decreased activity, and excessive scratching. In early clinical trials with daily subcutaneous leuprolide acetate, doses as high as 20 mg/day for up to two years caused no adverse effects differing from those observed with the 1 mg/day dose.

11 DESCRIPTION

Leuprolide acetate is a synthetic nonapeptide analog of naturally occurring gonadotropin-releasing hormone (GnRH). The analog possesses greater potency than the natural hormone. The chemical name is 5-oxo-L-prolyl-L-histidyl-L-tryptophyl-L-seryl-L-tyrosyl-D-leucyl-L-leucyl-L-arginyl-N-ethyl-L-prolinamide acetate (salt) with the following structural formula:

LUPRON DEPOT 7.5 mg for 1-month administration is available in a prefilled dual-chamber syringe containing sterile lyophilized microspheres which, when mixed with diluent, becomes a suspension intended as a monthly intramuscular injection.

The front chamber of LUPRON DEPOT 7.5 mg for 1-month administration prefilled dual-chamber syringe contains leuprolide acetate (7.5 mg), purified gelatin (1.3 mg), DL-lactic and glycolic acids copolymer (66.2 mg), and D-mannitol (13.2 mg). The second chamber of diluent contains carboxymethylcellulose sodium (5 mg), D-mannitol (50 mg), polysorbate 80 (1 mg), water for injection, USP, and glacial acetic acid, USP to control pH.

LUPRON DEPOT 22.5 mg for 3-month administration is available in a prefilled dual-chamber syringe containing sterile lyophilized microspheres which, when mixed with diluent, become a suspension intended as an intramuscular injection to be given ONCE EVERY 12 WEEKS.

The front chamber of LUPRON DEPOT 22.5 mg for 3-month administration prefilled dual-chamber syringe contains leuprolide acetate (22.5 mg), polylactic acid (198.6 mg) and D-mannitol (38.9 mg). The second chamber of diluent contains carboxymethylcellulose sodium (7.5 mg), D-mannitol (75.0 mg), polysorbate 80 (1.5 mg), water for injection, USP, and glacial acetic acid, USP to control pH.

LUPRON DEPOT 30 mg for 4-month administration is available in a prefilled dual-chamber syringe containing sterile lyophilized microspheres which, when mixed with diluent, become a suspension intended as an intramuscular injection to be given ONCE EVERY 16 WEEKS.

The front chamber of LUPRON DEPOT 30 mg for 4-month administration prefilled dual-chamber syringe contains leuprolide acetate (30 mg), polylactic acid (264.8 mg) and D-mannitol (51.9 mg). The second chamber of diluent contains carboxymethylcellulose sodium (7.5 mg), D-mannitol (75.0 mg), polysorbate 80 (1.5 mg), water for injection, USP, and glacial acetic acid, USP to control pH.

LUPRON DEPOT 45 mg for 6-month administration is available in a prefilled dual-chamber syringe containing sterile lyophilized microspheres which, when mixed with diluent, become a suspension intended as an intramuscular injection to be given ONCE EVERY 24 WEEKS.

The front chamber of LUPRON DEPOT 45 mg for 6-month administration prefilled dual-chamber syringe contains leuprolide acetate (45 mg), polylactic acid (169.9 mg), D-mannitol (39.7 mg), and stearic acid (10.1 mg). The second chamber of diluent contains carboxymethylcellulose sodium (7.5 mg), D-mannitol (75.0 mg), polysorbate 80 (1.5 mg), water for injection, USP, and glacial acetic acid, USP to control pH.

12 CLINICAL PHARMACOLOGY

12.1 Mechanism of Action

Leuprolide acetate, a GnRH agonist, acts as an inhibitor of gonadotropin secretion. Animal studies indicate that following an initial stimulation, continuous administration of leuprolide acetate results in suppression of ovarian and testicular steroidogenesis. This effect was reversible upon discontinuation of drug therapy.

Administration of leuprolide acetate has resulted in inhibition of the growth of certain hormone dependent tumors (prostatic tumors in Noble and Dunning male rats and DMBA-induced mammary tumors in female rats) as well as atrophy of the reproductive organs.

12.2 Pharmacodynamics

In humans, administration of leuprolide acetate results in an initial increase in circulating concentrations of luteinizing hormone (LH) and follicle stimulating hormone (FSH), leading to a transient increase in concentrations of the gonadal steroids (testosterone and dihydrotestosterone in males, and estrone and estradiol in premenopausal females). However, continuous administration of leuprolide acetate results in decreased concentrations of LH and FSH. In males, testosterone is reduced to castrate concentrations. In premenopausal females, estrogens are reduced to postmenopausal concentrations. These decreases occur within two to four weeks after initiation of treatment, and castrate concentrations of testosterone in prostatic cancer patients have been demonstrated for more than five years.

Leuprolide acetate is not active when given orally.

12.3 Pharmacokinetics

Absorption

LUPRON DEPOT 7.5 mg for 1-Month Administration

Following a single injection of LUPRON DEPOT 7.5 mg for 1-month administration to patients, mean plasma measured concentrations were 20 ng/mL at 4 hours and 0.36 ng/mL at 4 weeks. However, intact leuprolide and an inactive major metabolite could not be distinguished by the assay which was employed in the study.

LUPRON DEPOT 22.5 mg for 3-Month Administration

Following a single injection of LUPRON DEPOT 22.5 mg for 3-month administration in patients, mean peak plasma concentrations were 48.9 ng/mL at 4 hours and then declined to 0.67 ng/mL at 12 weeks. Leuprolide appeared to be released at a constant rate following the onset of steady-state concentrations during the third week after dosing, providing steady plasma concentrations through the 12-week dosing interval. However, intact leuprolide and an inactive major metabolite could not be distinguished by the assay which was employed in the study. The initial burst, followed by a decline to a steady-state concentration, was similar to the release pattern seen with the monthly formulation.

LUPRON DEPOT 30 mg for 4-Month Administration

Following a single injection of LUPRON DEPOT 30 mg for 4-month administration in sixteen orchiectomized prostate cancer patients, mean plasma concentrations were 59.3 ng/mL at 4 hours and then declined to 0.30 ng/mL at 16 weeks. Mean plasma concentrations from weeks 3.5 to 16 was 0.44 ± 0.20 ng/mL (range: 0.20-1.06). Leuprolide appeared to be released at a constant rate following the onset of steady-state concentrations during the fourth week after dosing, providing steady plasma concentrations throughout the 16-week dosing interval. However, intact leuprolide and an inactive major metabolite could not be distinguished by the assay which was employed in the study. The initial burst, followed by a decline to a steady-state concentration, was similar to the release pattern seen with the other depot formulations.

LUPRON DEPOT 45 mg for 6-Month Administration

Following a single injection of LUPRON DEPOT 45 mg for 6-month administration in 26 prostate cancer patients, mean peak plasma concentration of 6.7 ng/mL was observed at 2 hours and then declined to 0.07 ng/mL at 24 weeks. Leuprolide appeared to be released continuously following the onset of steady-state concentrations during the third week after dosing providing steady plasma concentrations through the 24-week dosing interval. The initial burst, followed by a decline to a steady-state concentration, was similar to the release pattern seen with the other depot formulations. In this study, mean plasma concentration-time profiles were similar after the first and second dose.

Distribution

The mean steady-state volume of distribution of leuprolide following intravenous bolus administration to healthy male volunteers was 27 L. In vitro binding to human plasma proteins ranged from 43% to 49%.

Elimination

The mean systemic clearance of leuprolide following intravenous bolus administration to healthy male volunteers was 7.6 L/h, and terminal elimination half-life was approximately 3 hours based on a two compartment model.

Following administration of LUPRON DEPOT 3.75 mg to 3 patients, less than 5% of the dose was recovered as parent and M-I metabolite in the urine.

13 NONCLINICAL TOXICOLOGY

13.1 Carcinogenesis, Mutagenesis, Impairment of Fertility

Two-year carcinogenicity studies were conducted with leuprolide acetate in rats and mice. In rats, a dose-related increase of benign pituitary hyperplasia and benign pituitary adenomas was noted at 24 months when the drug was administered subcutaneously at daily doses (0.6 to 4 mg/kg). There was a significant but not dose-related increase of pancreatic islet-cell adenomas in females and of testicular interstitial cell adenomas in males (highest incidence in the low dose group). In mice, no leuprolide acetate-induced tumors or pituitary abnormalities were observed at a dose as high as 60 mg/kg for two years. Patients have been treated with leuprolide acetate for up to three years with doses as high as 10 mg/day and for two years with doses as high as 20 mg/day without demonstrable pituitary abnormalities.

Genotoxicity studies were conducted with leuprolide acetate using bacterial and mammalian systems. These studies provided no evidence of mutagenic effects or chromosomal aberrations.

Leuprolide may reduce male and female fertility. Administration of leuprolide acetate to male and female rats at dose of 0.024, 0.24, and 2.4 mg/kg as monthly depot formulation for up to 3 months (approximately as low as 1/30 of the human dose based on body surface area using an estimated daily dose in animals and humans) caused atrophy of the reproductive organs, and suppression of reproductive function. These changes were reversible upon cessation of treatment.

14 CLINICAL STUDIES

14.1 LUPRON DEPOT 7.5 mg for 1-Month Administration

In an open-label, non-comparative, multicenter clinical study of LUPRON DEPOT 7.5 mg for 1-month administration, 56 patients with stage D2 prostatic adenocarcinoma and no prior systemic treatment were enrolled. The objectives were to determine if a 7.5 mg depot formulation of leuprolide injected once every 4 weeks would reduce and maintain serum testosterone to castrate range (≤50 ng/dL), to evaluate objective clinical response, and to assess the safety of the formulation. During the initial 24 weeks, serum testosterone was measured weekly, biweekly, or every four weeks and objective tumor response assessments were performed at Weeks 12 and 24. Once the patient completed the initial 24-week treatment phase, treatment continued at the investigator’s discretion. Data from the initial 24-week treatment phase are summarized in this section.

In the majority of patients, serum testosterone increased by 50% or more above baseline during the first week of treatment. Serum testosterone suppressed to the castrate range within 30 days of the initial depot injection in 94% (51/54) of patients for whom testosterone suppression was achieved (2 patients withdrew prior to onset of suppression) and within 66 days in all 54 patients. Mean serum testosterone suppressed to castrate level by Week 3. The median dosing interval between injections was 28 days. One escape from suppression (2 consecutive testosterone values greater than 50 ng/dL after achieving castrate level) was noted at Week 18, associated with a substantial dosing delay. In this patient, serum testosterone returned to the castrate range at the next monthly measurement. Serum testosterone was minimally above the castrate range on a single occasion for 4 other patients. No clinical significance was attributed to these rises in testosterone.

Figure 8. LUPRON DEPOT 7.5 mg for 1-Month Administration Mean Serum Testosterone Concentrations

Secondary efficacy endpoints evaluated included objective tumor response, assessed by clinical evaluations of tumor burden (complete response, partial response, objectively stable, and progression), as well as changes in local disease status, assessed by digital rectal examination, and changes in prostatic acid phosphatase (PAP). These evaluations were performed at Weeks 12 and 24. The objective tumor response analysis showed a “no progression” (i.e. Complete or partial response, or stable disease) in 77% (40/52) of patients at Week 12, and in 84% (42/50) of patients at Week 24. Local disease improved or remained stable in all (42) patients evaluated at Week 12 and in 98% (41/42) of patients elevated at Week 24. PAP normalized or decreased at Week 12 and/or 24 in the majority of patients with elevated baseline PAP.

Periodic monitoring of serum testosterone and PSA levels is recommended, especially if the anticipated clinical or biochemical response to treatment has not been achieved. It should be noted that results of testosterone determinations are dependent on assay methodology. It is advisable to be aware of the type and precision of the assay methodology to make appropriate clinical and therapeutic decisions.

14.2 LUPRON DEPOT 22.5 mg for 3-Month Administration

In clinical studies, serum testosterone was suppressed to castrate within 30 days in 87 of 92 (95%) patients and within an additional two weeks in three patients. Two patients did not suppress for 15 and 28 weeks, respectively. Suppression was maintained in all of these patients with the exception of transient minimal testosterone elevations in one of them, and in another an increase in serum testosterone to above the castrate range was recorded during the 12 hour observation period after a subsequent injection. This represents stimulation of gonadotropin secretion.

Figure 9. LUPRON DEPOT 22.5 mg for 3-Month Administration Mean Serum Testosterone Concentrations

An 85% rate of “no progression” was achieved during the initial 24 weeks of treatment. A decrease from baseline in serum PSA of ≥90% was reported in 71% of the patients and a change to within the normal range (≤3.99 ng/mL) in 63% of the patients.

Periodic monitoring of serum testosterone and PSA levels is recommended, especially if the anticipated clinical or biochemical response to treatment has not been achieved. It should be noted that results of testosterone determinations are dependent on assay methodology. It is advisable to be aware of the type and precision of the assay methodology to make appropriate clinical and therapeutic decisions.

14.3 LUPRON DEPOT 30 mg for 4-Month Administration

In an open-label, noncomparative, multicenter clinical study of LUPRON DEPOT 30 mg for 4-month administration, 49 patients with stage D2 prostatic adenocarcinoma (with no prior treatment) were enrolled. The objectives were to determine whether a 30 mg depot formulation of leuprolide injected once every 16 weeks would reduce and maintain serum testosterone levels at castrate levels (≤ 50 ng/dL), and to assess the safety of the formulation. The study was divided into an initial 32-week treatment phase and a long-term treatment phase. Serum testosterone levels were determined biweekly or weekly during the first 32 weeks of treatment. Once the patient completed the initial 32-week treatment period, treatment continued at the investigator’s discretion with serum testosterone levels being done every 4 months prior to the injection.

In the majority of patients, testosterone levels increased 50% or more above the baseline during the first week of treatment. Mean serum testosterone subsequently suppressed to castrate levels within 30 days of the first injection in 94% of patients and within 43 days in all 49 patients during the initial 32-week treatment period. The median dosing interval between injections was 112 days. One escape from suppression (two consecutive testosterone values greater than 50 ng/dL after castrate levels achieved) was noted at Week 16. In this patient, serum testosterone increased to above the castrate range following the second depot injection (Week 16) but returned to the castrate level by Week 18. No adverse reactions were associated with this rise in serum testosterone. A second patient had a rise in testosterone at Week 17, then returned to the castrate level by Week 18 and remained there through Week 32. In the long-term treatment phase two patients experienced testosterone elevations, both at Week 48. Testosterone for one patient returned to the castrate range at Week 52, and one patient discontinued the study at Week 48 due to disease progression.

Secondary efficacy endpoints evaluated in the study were the objective tumor response as assessed by clinical evaluations of tumor burden (complete response, partial response, objectively stable and progression) and evaluations of changes in prostatic involvement and prostate-specific antigen (PSA). These evaluations were performed at Weeks 16 and 32 of the treatment phase. The long-term treatment phase monitored PSA at each visit (every 16 weeks). The objective tumor response analysis showed “no progression” (i.e. complete or partial response, or stable disease) in 86% (37/43) of patients at Week 16, and in 77% (37/48) of patients at Week 32. Local disease improved or remained stable in all patients evaluated at Week 16 and/or 32. For patients with elevated baseline PSA, 50% (23/46) had a normal PSA (less than 4.0 ng/mL) at Week 16, and 51% (19/37) had a normal PSA at Week 32.

Periodic monitoring of serum testosterone and PSA levels is recommended, especially if the anticipated clinical or biochemical response to treatment has not been achieved. It should be noted that results of testosterone determinations are dependent on assay methodology. It is advisable to be aware of the type and precision of the assay methodology to make appropriate clinical and therapeutic decisions.

Using historical comparisons, the safety and efficacy of LUPRON DEPOT 30 mg for 4-month administration appear similar to the other LUPRON DEPOT formulations.

Figure 10. LUPRON DEPOT 30 mg for 4-Month Administration Mean Serum Testosterone Concentrations

14.4 LUPRON DEPOT 45 mg for 6-Month Administration

An open-label, non-comparative, multicenter clinical study of LUPRON DEPOT 45 mg for 6-month administration enrolled 151 patients with prostate cancer. The study drug was administered as two intramuscular injections of LUPRON DEPOT 45 mg at 24 week intervals (139/151 received 2 injections), and patients were followed for a total of 48 weeks.

Among 148 patients who had testosterone value at Week 4, serum testosterone was suppressed to castrate levels (< 50 ng/dL) from Week 4 through Week 48 in an estimated 93.4% (two-sided 95% CI: 89.2%, 97.6%) of patients. One patient failed to achieve testosterone suppression by Week 4, and eight patients had escapes from suppression (any testosterone value > 50 ng/dL after castrate levels were achieved). Mean testosterone levels increased to 608 ng/dL from a baseline of 435 ng/dL during the first week of treatment. By Week 4, the mean testosterone concentration had decreased to below castrate levels (16 ng/dL).

Periodic monitoring of serum testosterone levels is recommended, especially if the anticipated clinical or biochemical response to treatment has not been achieved. Testosterone determinations are dependent on assay methodology and it is advisable to be aware of the type and precision of the assay methodology to make appropriate clinical and therapeutic decisions.

Figure 11 below shows the mean testosterone concentration at various time points.

Figure 11. LUPRON DEPOT 45 mg for 6-Month Administration Serum Testosterone Concentrations (Mean + SE)

15 REFERENCES

1. “OSHA Hazardous Drugs.” OSHA. http://www.osha.gov/SLTC/hazardousdrugs/index.html

16 HOW SUPPLIED/STORAGE AND HANDLING

Each LUPRON DEPOT kit contains:

- one prefilled dual-chamber syringe containing needle with LuproLoc® safety device
- one plunger
- two alcohol swabs

a complete prescribing information enclosure

Strength | Frequency of Administration | Description | NDC Number
7.5 mg | Every month | Single-dose prefilled dual-chamber syringe containing sterile white lyophilized microspheres of leuprolide acetate incorporated in a biodegradable lactic acid/glycolic acid copolymer to be mixed with 1 mL of accompanying clear, colorless diluent. | 0074-3642-03
22.5 mg | Every 3 months | Single-dose prefilled dual-chamber syringe containing sterile white lyophilized microspheres of leuprolide acetate incorporated in a biodegradable lactic acid polymer to be mixed with 1.5 mL of accompanying clear, colorless diluent. | 0074-3346-03
30 mg | Every 4 months | Single-dose prefilled dual-chamber syringe containing sterile white lyophilized microspheres of leuprolide acetate incorporated in a biodegradable lactic acid polymer to be mixed with 1.5 mL of accompanying clear, colorless diluent. | 0074-3683-03
45 mg | Every 6 months | Single-dose prefilled dual-chamber syringe containing sterile white lyophilized microspheres of leuprolide acetate incorporated in a biodegradable lactic acid polymer to be mixed with 1.5 mL of accompanying clear, colorless diluent. | 0074-3473-03

Store between 20° to 25°C (68° to 77°F); excursions permitted to 15°C to 30°C (59°F to 86°F) [See USP Controlled Room Temperature].

17 PATIENT COUNSELING INFORMATION

Hypersensitivity Reactions

- Inform patients that if they have experienced hypersensitivity with other GnRH agonist drugs like LUPRON DEPOT, LUPRON DEPOT is contraindicated [see Contraindications (4)].

Tumor Flare

- Inform patients that LUPRON DEPOT can cause tumor flare during the first weeks of treatment. Inform patients that the increase in testosterone can cause an increase in urinary symptoms or pain. Advise patients to contact their healthcare provider if bone pain, neuropathy, hematuria, bladder outlet obstruction, spinal cord compression, or new or worsened symptoms occur after beginning LUPRON DEPOT treatment [see Warnings and Precautions (5.1)].

Metabolic Syndrome

- Advise patients that there is an increased risk of metabolic changes such as hyperglycemia, diabetes, hyperlipidemia, and non-alcoholic fatty liver disease with LUPRON DEPOT therapy. Inform patients that periodic monitoring for metabolic changes is required when being treated with LUPRON DEPOT [see Warnings and Precautions (5.2)].

Cardiovascular Disease

- Inform patients that there is an increased risk of myocardial infarction, sudden cardiac death, and stroke with LUPRON DEPOT treatment. Advise patients to immediately report signs and symptoms associated with these events to their healthcare provider for evaluation [see Warnings and Precautions (5.3)].

Severe Cutaneous Adverse Reactions

- Inform patients that severe cutaneous adverse reactions (SCARs), including Stevens-Johnson syndrome (SJS), toxic epidermal necrolysis (TEN), drug reaction with eosinophilia and systemic symptoms (DRESS), and acute generalized exanthematous pustulosis (AGEP), which may be life threatening or fatal, may occur during treatment with LUPRON DEPOT. Advise patients to contact their healthcare provider or seek medical attention right away if they experience signs or symptoms of SCARs [see Warnings and Precautions (5.6)].

Injection Site Reactions

- Inform patients and caregivers that injection site reactions such as pain, induration, abscess, and necrosis may occur with LUPRON DEPOT. Advise patients to contact their healthcare provider if they experience injection site reactions [see Adverse Reactions (6.4, 6.5)].

Urogenital Disorders

- Advise patients that LUPRON DEPOT may cause impotence [see Adverse Reactions (6)].

Infertility

- Inform patients that LUPRON DEPOT may cause infertility [see Use in Specific Populations (8.3)].

Continuation of LUPRON DEPOT Treatment

- Inform patients that LUPRON DEPOT is usually continued, often with additional medication, after the development of non-metastatic and metastatic castration-resistant prostate cancer [see Dosage and Administration (2.1)].

Manufactured for
AbbVie Inc.
North Chicago, IL 60064
by Takeda Pharmaceutical Company Limited
Osaka, Japan 540-8645

20093533

PACKAGE LABEL

NDC 0074-3473-03

FOR ADULT USE

45 mg for 6-month administration

Single Dose Administration Kit with prefilled dual-chamber syringe.

LupronDepot®

(Leuprolide Acetate for Depot Suspension)

45 mg for 6-month administration

FOR INTRAMUSCULAR INJECTION

The front chamber contains: leuprolide acetate 45 mg

• polylactic acid 169.9 mg • D-mannitol 39.7 mg • stearic acid 10.1 mg

The second chamber contains: carboxymethylcellulose sodium 7.5 mg

• D-mannitol 75.0 mg • polysorbate 80 1.5 mg • water for injection, USP,

and glacial acetic acid, USP to control pH

Rx only

PACKAGE LABEL

NDC 0074-3346-03

FOR ADULT USE

22.5 mg for 3-month

Single Dose Administration Kit with prefilled dual-chamber syringe.

LupronDepot®

(Leuprolide Acetate for Depot Suspension)

22.5 mg for 3-month administration

FOR INTRAMUSCULAR INJECTION

The front chamber contains: leuprolide acetate 22.5 mg

• polylactic acid 198.6 mg • D-mannitol 38.9 mg

The second chamber contains: carboxymethylcellulose sodium 7.5 mg

• D-mannitol 75.0 mg • polysorbate 80 1.5 mg • water for injection, USP,

and glacial acetic acid, USP to control pH

Rx only

PACKAGE LABEL

NDC 0074-3683-03

FOR ADULT USE

30 mg for 4-month administration

Single Dose Administration Kit with prefilled dual-chamber syringe.

LupronDepot®

(Leuprolide Acetate for Depot Suspension)

30 mg for 4-month administration

FOR INTRAMUSCULAR INJECTION

The front chamber contains: leuprolide acetate 30 mg

• polylactic acid 264.8 mg • D-mannitol 51.9 mg

The second chamber contains: carboxymethylcellulose sodium 7.5 mg

• D-mannitol 75.0 mg • polysorbate 80 1.5 mg • water for injection, USP,

and glacial acetic acid, USP to control pH

Rx only

PACKAGE LABEL

NDC 0074–3642–03

FOR ADULT USE 7.5 mg for 1–month administration

Single Dose Administration Kit with prefilled dual-chamber syringe.

LupronDepot®

(Leuprolide Acetate for Depot Suspension)

7.5 mg for 1–month administration

FOR INTRAMUSCULAR INJECTION

The front chamber contains: leuprolide acetate 7.5 mg • purified gelatin 1.3 mg • DL-lactic and glycolic acids copolymer 66.2 mg • D-mannitol 13.2 mg

The second chamber contains: carboxymethylcellulose sodium 5 mg • D-mannitol 50 mg • polysorbate 80 1 mg • water for injection, USP, and glacial acetic acid, USP to control pH

Rx only